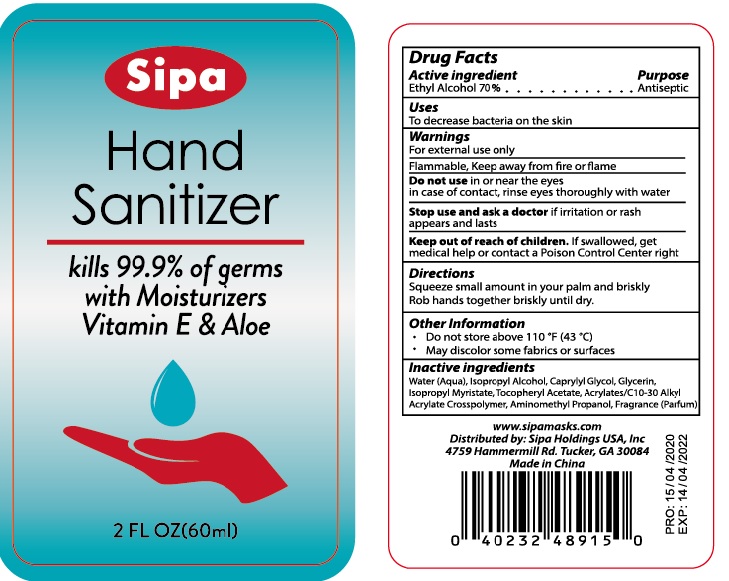 DRUG LABEL: Sipa Hand Sanitizer with Moisturizers Vitamin E and Aloe
NDC: 75780-006 | Form: GEL
Manufacturer: Ningbo Mannike Biological Technology Co., Ltd.
Category: otc | Type: HUMAN OTC DRUG LABEL
Date: 20200521

ACTIVE INGREDIENTS: alcohol 70 mL/100 mL
INACTIVE INGREDIENTS: WATER; CAPRYLYL GLYCOL; ALOE VERA LEAF; ISOPROPYL MYRISTATE; GLYCERIN; AMINOMETHYLPROPANOL; CARBOMER COPOLYMER TYPE A

Drug facts

Active ingredient Purpose

Ethyl Alcohol 70% ... Antiseptic

PURPOSE

To decrease bacteria on the skin

KEEP OUT OF REACH OF CHILDREN

If swallowed, get meical help or contact Poison Control Center right away.

INDICATIONS AND USAGE

Squeeze small amount in your palm and briskly

Rob hands together briskly until dry

WARNINGS

For external use only.
Flammable. Keep away from fire or flame.

Do not use:

- in or near the eyes, In case of contact, rinse eyes thoroughly with water

Stop use and ask a doctor

If irritation or rash appears and lasts

Other information:

- Store between 59°-86℉ （15°-30℃）
- Avoid freezing and excessive heat above 104℉ （40℃）

INACTIVE INGREDIENT

Water (Aqua), Isoprcpyl Alcohol, Caprylyl Glycol, Glycerin, Isopropyl Myristate, Tocopheryl Acetate, Acrylates/C10-30 Alkyl Acrylate Crosspolymer, Aminomethyl Propanol, Fragrance (Parfum)